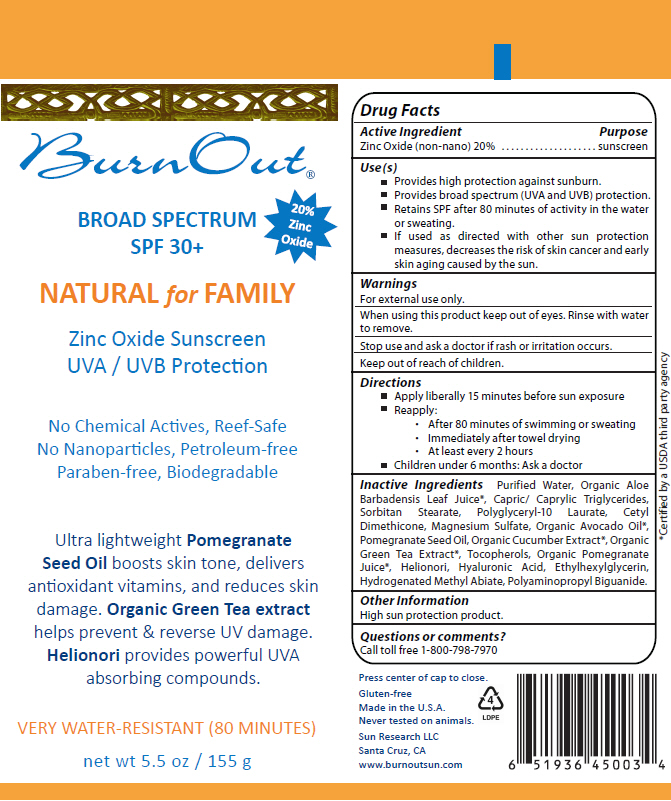 DRUG LABEL: Natural for Family SPF 30
NDC: 55777-0200 | Form: LOTION
Manufacturer: Sun Research LLC
Category: otc | Type: HUMAN OTC DRUG LABEL
Date: 20200121

ACTIVE INGREDIENTS: Zinc Oxide 200 mg/1 g
INACTIVE INGREDIENTS: Water; Sorbitan Monostearate; Polyglyceryl-10 Laurate; Magnesium Sulfate, Unspecified Form; Tocopherol; Hyaluronic Acid; Ethylhexylglycerin

Natural for Family SPF 30

Drug Facts

Active Ingredient

Zinc Oxide (non-nano) 20%

Purpose

sunscreen

Use(s)

- Provides high protection against sunburn.
- Provides broad spectrum (UVA and UVB) protection.
- Retains SPF after 80 minutes of activity in the water or sweating.
- If used as directed with other sun protection measures, decreases the risk of skin cancer and early skin aging caused by the sun.

Warnings

For external use only.

When using this product keep out of eyes. Rinse with water to remove.

Stop use and ask a doctor if rash or irritation occurs.

Keep out of reach of children.

Directions

- Apply liberally 15 minutes before sun exposure
- Reapply:
  - After 80 minutes of swimming or sweating
  - Immediately after towel drying
  - At least every 2 hours
- Children under 6 months: Ask a doctor

Inactive Ingredients

Purified Water, Organic Aloe Barbadensis Leaf Juice [Certified by a USDA third party agency] , Capric/ Caprylic Triglycerides, Sorbitan Stearate, Polyglyceryl-10 Laurate, Cetyl Dimethicone, Magnesium Sulfate, Organic Avocado Oil, Pomegranate Seed Oil, Organic Cucumber Extract, Organic Green Tea Extract, Tocopherols, Organic Pomegranate Juice, Helionori, Hyaluronic Acid, Ethylhexylglycerin, Hydrogenated Methyl Abiate, Polyaminopropyl Biguanide.

Other Information

High sun protection product.

Questions or comments?

Call toll free 1-800-798-7970

PRINCIPAL DISPLAY PANEL - 155 g Tube Label

BurnOut®

BROAD SPECTRUM
SPF 30+

20%
Zinc
Oxide

NATURAL for FAMILY

Zinc Oxide Sunscreen
UVA / UVB Protection

No Chemical Actives, Reef-Safe
No Nanoparticles, Petroleum-free
Paraben-free, Biodegradable

Ultra lightweight Pomegranate
Seed Oil boosts skin tone, delivers
antioxidant vitamins, and reduces skin
damage. Organic Green Tea extract
helps prevent & reverse UV damage.
Helionori provides powerful UVA
absorbing compounds.

VERY WATER-RESISTANT (80 MINUTES)

net wt 5.5 oz / 155 g